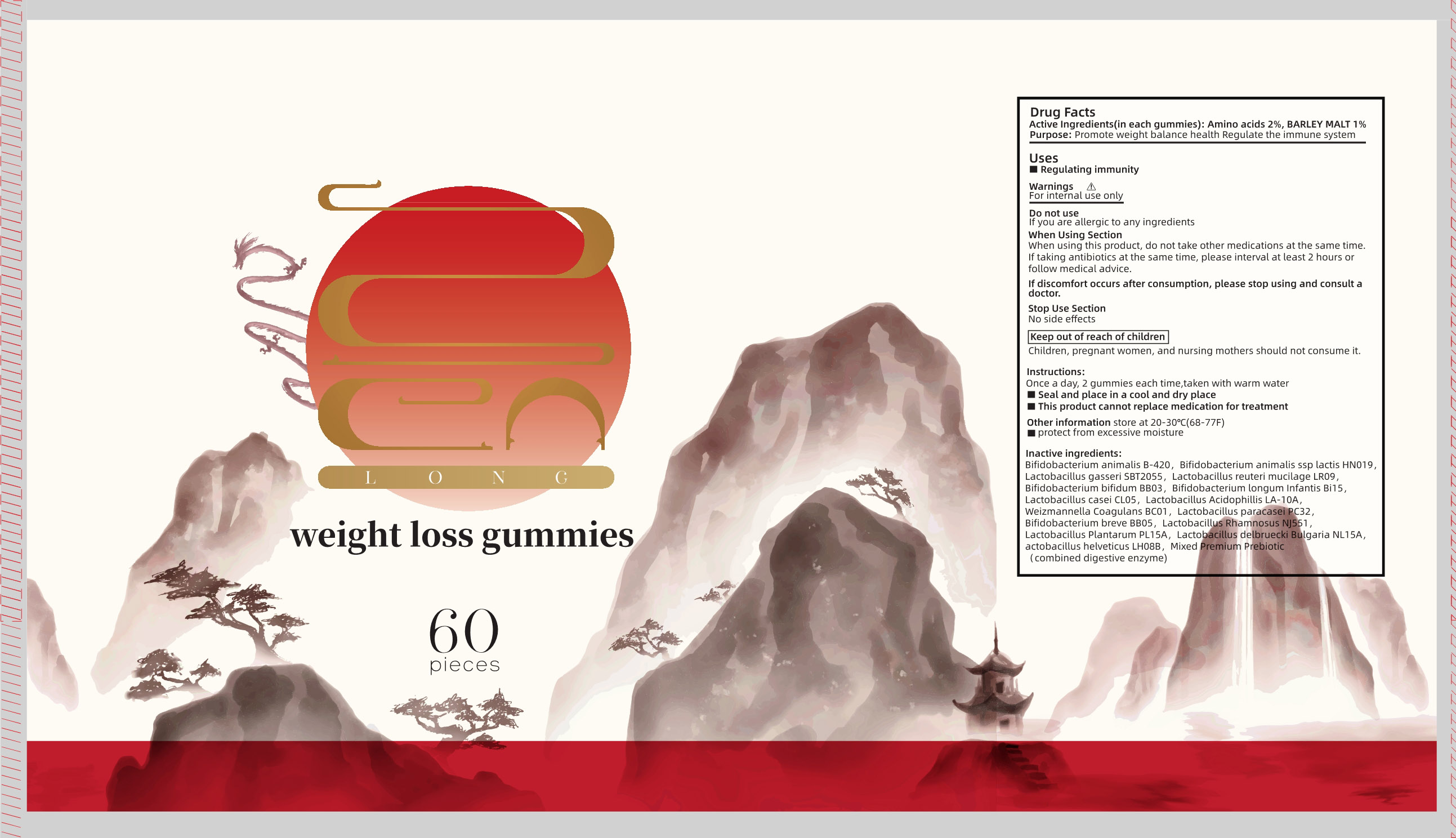 DRUG LABEL: weight loss gummies
NDC: 83739-007 | Form: CHEWABLE GEL
Manufacturer: XIAN CHIANG COMPANY LIMITED
Category: otc | Type: HUMAN OTC DRUG LABEL
Date: 20250216

ACTIVE INGREDIENTS: AMINO ACIDS 2 g/100 1; BARLEY MALT 1 g/100 1
INACTIVE INGREDIENTS: BIFIDOBACTERIUM ANIMALIS LACTIS B420; BIFIDOBACTERIUM LONGUM INFANTIS; LACTOBACILLUS ACIDOPHILUS; LACTICASEIBACILLUS RHAMNOSUS; BIFIDOBACTERIUM ANIMALIS; LIMOSILACTOBACILLUS REUTERI; BIFIDOBACTERIUM BIFIDUM; BIFIDOBACTERIUM BREVE; LACTIPLANTIBACILLUS PLANTARUM; LACTOBACILLUS GASSERI; LACTOBACILLUS HELVETICUS; LACTICASEIBACILLUS CASEI; LACTICASEIBACILLUS PARACASEI; LACTOBACILLUS DELBRUECKII BULGARICUS

83739-007

ACTIVE INGREDIENT

Amino acids 2%, BARLEY MALT 1%

Purpose

Promote weight balance health Regulate the immune system

Uses

Regulating immunity

Warnings

For internal use only

Do not use

If you are allergic to any ingredients

When Using Section

When using this product , do not take other medications at the same timeIf taking antibiotics at the same time , If taking antibiotics at the same time, please interval at least 2 hours or follow medical advice.

If discomfort occurs after consumption , please stop using and consult a doctor

Stop Use section

No side effects

Keep out of reach of children

Children , pregnant women , and nursing mothers should not consume it .

Instructions

Once a day , 2 gummies each time , taken with warm water

Seal and place in a cool and dry place

This product cannot replace medication for treatment

Other information

Other information store at 20-30°C(68-77F)

protect from excessive moisture

Inactive ingredients

Bifidobacterium animalis B-420 , Bifidobacterium animalis ssp lactis HN019, Lactobacillus gasseri SBT2055 , Lactobacillus reuteri mucilage LR09, Bifidobacterium bifidum BB03 , Bifidobacterium longum Infantis Bi15, Lactobacillus Casei CL05 , Lactobacillus Acidophillis LA-10A, Weizmannella Coagulans BC01 , Lactobacillus paracasei PC32, Bifidobacterium breve BB05 , Lactobacillus Rhamnosus NJ551, Lactobacillus Plantarum PL15A , Lactobacillus delbruecki Bulgaria NL15A, Lactobacillus helveticus LH08B , Mixed Premium Prebiotic(combined digestive enzyme)